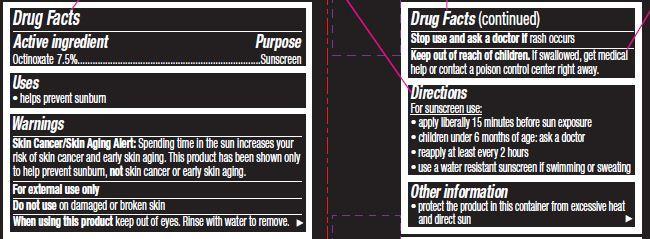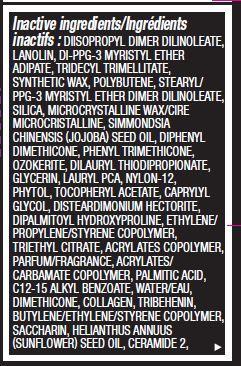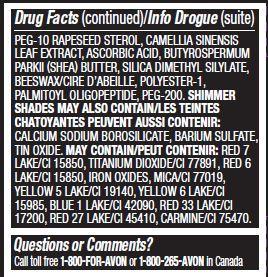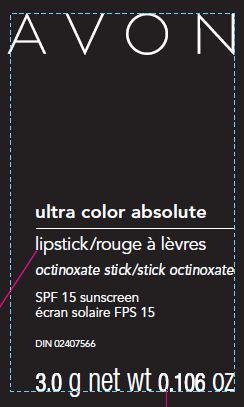 DRUG LABEL: ultra color absolute
NDC: 10096-0325 | Form: LIPSTICK
Manufacturer: New Avon LLC
Category: otc | Type: HUMAN OTC DRUG LABEL
Date: 20160219

ACTIVE INGREDIENTS: OCTINOXATE 75 mg/1 g

Active ingredient
Octinoxate 7.5%.............................................

Purpose
.................................Sunscreen

Uses
• helps prevent sunburn

Warnings

Skin Cancer/Skin Aging Alert: Spending time in the sun increases your risk of skin cancer and early skin aging. This product has been shown only to help prevent sunburn, not skin cancer or early skin aging.
For external use only

Do not use on damaged or broken skin

When using this product keep out of eyes. Rinse with water to remove.

Stop use and ask a doctor if rash occurs

Keep out of reach of children. If swallowed, get medical help or contact a Poison Control Center right away.

Directions

For sunscreen use:
• apply liberally 15 minutes before sun exposure
• children under 6 months of age: ask a doctor
• reapply at least every 2 hours
• use a water resistant sunscreen if swimming or sweating

Other information

• protect the product in this container from excessive heat and direct sun

Inactive Ingredients:
DIISOPROPYL DIMER DILINOLEATE, LANOLIN, DI-PPG-3 MYRISTYL ETHER ADIPATE, TRIDECYL TRIMELLITATE, SYNTHETIC WAX, POLYBUTENE, STEARYL/PPG-3 MYRISTYL ETHER DIMER DILINOLEATE, SILICA, MICROCRYSTALLINE WAX/CIRE MICROCRISTALLINE, SIMMONDSIA CHINENSIS (JOJOBA) SEED OIL, DIPHENYL DIMETHICONE, PHENYL TRIMETHICONE, OZOKERITE, DILAURYL THIODIPROPIONATE, GLYCERIN, LAURYL PCA, NYLON-12, PHYTOL, TOCOPHERYL ACETATE, CAPRYLYL GLYCOL, DISTEARDIMONIUM HECTORITE, DIPALMITOYL HYDROXYPROLINE, ETHYLENE/
PROPYLENE/STYRENE COPOLYMER, TRIETHYL CITRATE, ACRYLATES COPOLYMER, PARFUM/FRAGRANCE, ACRYLATES/CARBAMATE COPOLYMER, PALMITIC ACID, C12-15 ALKYL BENZOATE, WATER/EAU, DIMETHICONE, COLLAGEN, TRIBEHENIN, BUTYLENE/ETHYLENE/STYRENE COPOLYMER,
SACCHARIN, HELIANTHUS ANNUUS (SUNFLOWER) SEED OIL, CERAMIDE 2, PEG-10 RAPESEED STEROL, CAMELLIA SINENSIS LEAF EXTRACT, ASCORBIC ACID, BUTYROSPERMUM PARKII (SHEA) BUTTER, SILICA DIMETHYL SILYLATE, BEESWAX/CIRE D’ABEILLE, POLYESTER-1, PALMITOYL OLIGOPEPTIDE, PEG-200. SHIMMER SHADES MAY ALSO CONTAIN: CALCIUM SODIUM BOROSILICATE, BARIUM SULFATE, TIN OXIDE. MAY CONTAIN: RED 7 LAKE/CI 15850, TITANIUM DIOXIDE/CI 77891, RED 6 LAKE/CI 15850, IRON OXIDES, MICA/CI 77019, YELLOW 5 LAKE/CI 19140, YELLOW 6 LAKE/CI 15985, BLUE 1 LAKE/CI 42090, RED 33 LAKE/CI 17200, RED 27 LAKE/CI 45410, CARMINE/CI 75470.

Questions or Comments?
Call toll free 1-800-FOR-AVON or 1-800-265-AVON in Canada